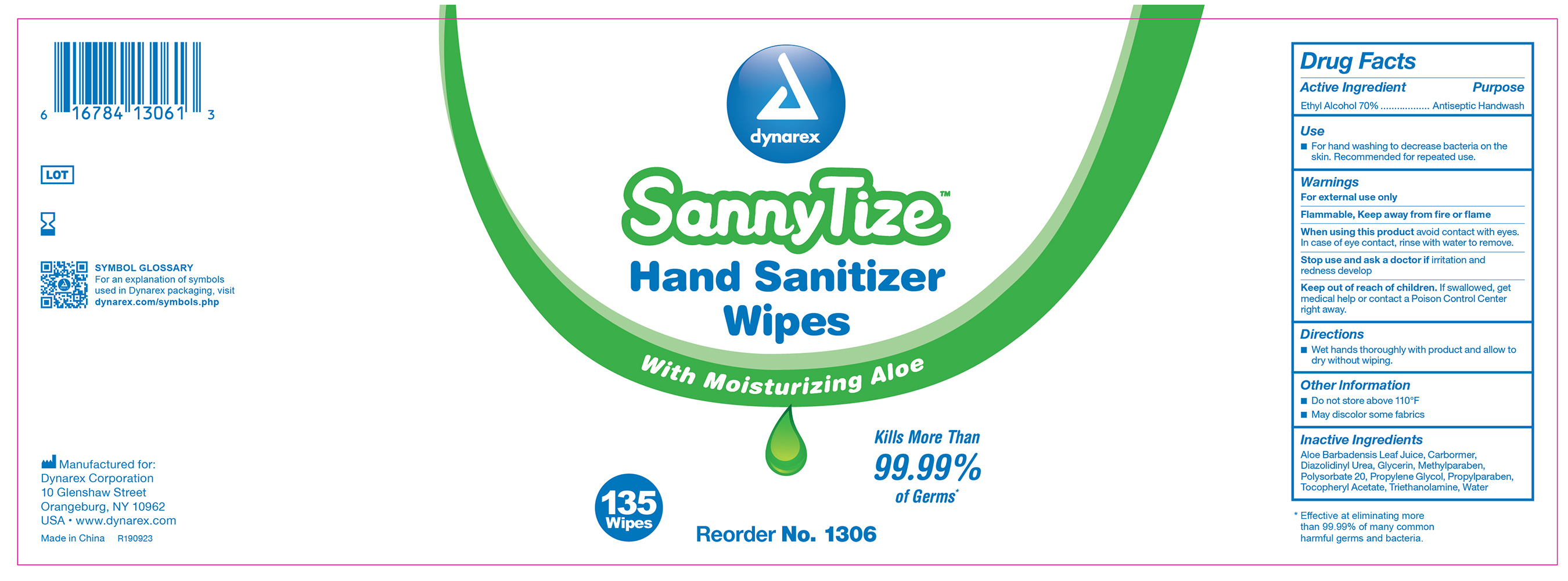 DRUG LABEL: SannyTize Hand Sanitizer Wipe
NDC: 67777-320 | Form: GEL
Manufacturer: Dynarex Corporation
Category: otc | Type: HUMAN OTC DRUG LABEL
Date: 20241120

ACTIVE INGREDIENTS: ALCOHOL 0.7 mL/1 mL
INACTIVE INGREDIENTS: WATER; GLYCERIN; PROPYLENE GLYCOL; ALOE VERA LEAF; .ALPHA.-TOCOPHEROL ACETATE; POLYSORBATE 20; DIAZOLIDINYL UREA; PROPYLPARABEN; METHYLPARABEN; CARBOMER HOMOPOLYMER, UNSPECIFIED TYPE; TROLAMINE

1306 Dynarex SannyTize Hand Sanitizer Wipes NDC 67777-320-01

ACTIVE INGREDIENT

Active Ingredient Purpose

Ethyl Alcohol 70% Antiseptic Wipe

WARNINGS

- For external use only
- Flammable, keep away from fire and flame
- When using this product avoid contact with eyes. In case of eye contact, rinse with water to remove.
- Stop use and ask a doctor if irritation and redness develops

PURPOSE

Antiseptic handwash

INDICATIONS & USAGE

For hand washing to decrease bacteria on the skin. Recommended for repeated use.

DOSAGE & ADMINISTRATION

Wet hands thoroughly with product and allow to dry without wiping.

KEEP OUT OF REACH OF CHILDREN, if swallowed get medical help or contact a Poison Control Center right away.

INACTIVE INGREDIENTS

Inactive ingredients: Water, Glycerin, Propylene glycol, Diazolidinyl urea, Aloe barbadensis leaf juice, Polysorbate 20, Carbomer, Tocopherol acetate, Methylparaben, Propylparaben, Triethanolamine

RECENT MAJOR CHANGES

- Content of Labeling

- Indications and Usage Section

- Date Incorporated 09/2020

- Content of labeling

- Dosage and Administration Section

- Date incorporated 09/2020

PRINCIPAL DISPLAY PANEL

Dynarex SannyTizer HandSanitizing Wipes

Sannywipe.jpg